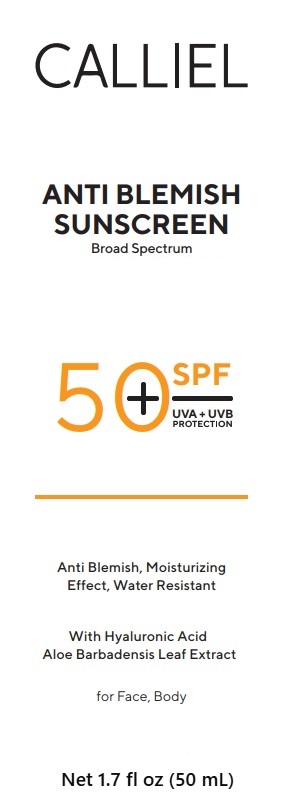 DRUG LABEL: CALLIEL Antiblemish Sunscreen SPF 50
NDC: 87411-0004 | Form: CREAM
Manufacturer: CALLIEL PHARMA KOZMETIK SANAYI VE TICARET ANONIM SIRKETI
Category: otc | Type: HUMAN OTC DRUG LABEL
Date: 20260207

ACTIVE INGREDIENTS: AVOBENZONE 2.7 g/100 g; HOMOSALATE 9.5 g/100 g; OCTINOXATE 7.2 g/100 g; OCTOCRYLENE 9.5 g/100 g; ZINC OXIDE 0.32 g/100 g
INACTIVE INGREDIENTS: XYLITYLGLUCOSIDE 1.65 g/100 g; HYALURONIC ACID 1.52 g/100 g; DIMETHICONE 2 g/100 g; 2-ETHYLHEXYL ACRYLATE, METHACRYLATE, METHYL METHACRYLATE, OR BUTYL METHACRYLATE/HYDROXYPROPYL DIMETHICONE COPOLYMER (30000-300000 MW) 2.1 g/100 g; NIACINAMIDE 2.1 g/100 g; C12-15 ALKYL BENZOATE 7 g/100 g; CAPRYLIC/CAPRIC TRIGLYCERIDE 2.1 g/100 g; PHENOXYETHANOL 1.1 g/100 g; GLYCERIN 2.1 g/100 g; CETEARETH-20 4.1 g/100 g; BUTYROSPERMUM PARKII (SHEA) BUTTER 6.5 g/100 g; GLYCERYL STEARATE 4.1 g/100 g; WATER 27.51 g/100 g; CETEARYL ALCOHOL 6.7 g/100 g

Active ingredients

Avobenzone 2.7%
Zinc Oxide 0.32%
Octocrylene 9.5%
Octinoxate 7.2%
Homosalate 9.5%

Uses

• helps prevent sunburn
• if used as directed with other sun protection measures (see Directions), decreases the risk of skin cancer and early skin aging caused by the sun

Do not use on damaged or broken skin

Stop use and ask a doctor if rash occurs.

Keep out of reach of children. If swallowed, get medical help or contact a Poison Control Center right away.

Directions

• apply liberally 15 minutes before sun exposure
• reapply:
• after 80 minutes of swimming or sweating
• immediately after towel drying
• at least every 2 hours
• children under 6 months: Ask a doctor

Sun Protection Measures: Spending time in the sun increases your risk of skin cancer and early skin aging caused by the sun. To decrease this risk, regularly use a sunscreen with a Broad Spectrum SPF 15 or higher and other sun protection measures including:
• limit time in the sun, especially from 10 a.m. – 2 p.m.
• wear long-sleeve shirts, pants, hats, and sunglasses

Warnings

For external use only

Purpose

Sunscreen

Inactive ingredients

Xylitylglucoside, Hyaluronic Acid, Dimethicone, 2-Ethylhexyl Acrylate, Methacrylate, Methyl Methacrylate, or Butyl Methacrylate/Hydroxypropyl Dimethicone Copolymer (3000000 MW), Niacinamide, C12-15 Alkyl Benzoate, Caprylic/Capric Triglyceride, Phenoxyethanol, Glycerin, Ceteareth-20, Butyrospermum Parkii (Shea) Butter, Glyceryl Stearate, Water, Cetearyl Alcohol.

PACKAGE LABEL

CALLIEL

SUNSCREEN SPF 50

Broad Spectrum SPF 50

Water Resistant (80 minutes)

Net 1.7 fl oz (50 mL)